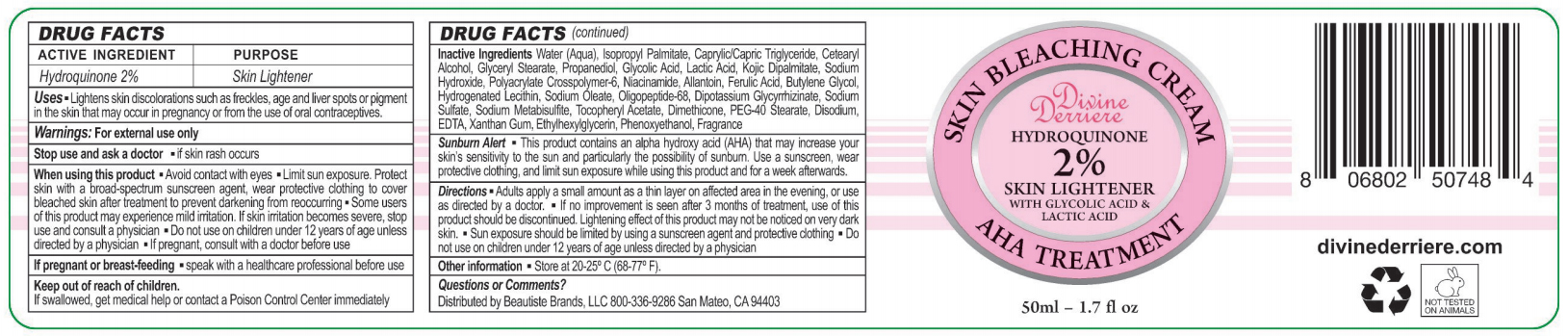 DRUG LABEL: Divine Derrier Skin Bleaching cream
NDC: 56152-4004 | Form: CREAM
Manufacturer: Cosmetic Enterprises Ltd
Category: otc | Type: HUMAN OTC DRUG LABEL
Date: 20190107

ACTIVE INGREDIENTS: HYDROQUINONE 2 g/100 mL
INACTIVE INGREDIENTS: WATER; CETOSTEARYL ALCOHOL; GLYCERYL MONOSTEARATE; PROPANEDIOL; GLYCOLIC ACID; NIACINAMIDE; XANTHAN GUM; ALLANTOIN; FERULIC ACID; SODIUM OLEATE; GLYCYRRHIZINATE DIPOTASSIUM; PEG-40 STEARATE; EDETATE DISODIUM; BUTYLENE GLYCOL; .ALPHA.-TOCOPHEROL ACETATE; KOJIC DIPALMITATE; SODIUM HYDROXIDE; LACTIC ACID; PHENOXYETHANOL; SODIUM SULFATE; SODIUM METABISULFITE; DIMETHICONE; ETHYLHEXYLGLYCERIN; MEDIUM-CHAIN TRIGLYCERIDES; HYDROGENATED SOYBEAN LECITHIN; AMMONIUM ACRYLOYLDIMETHYLTAURATE, DIMETHYLACRYLAMIDE, LAURYL METHACRYLATE AND LAURETH-4 METHACRYLATE COPOLYMER, TRIMETHYLOLPROPANE TRIACRYLATE CROSSLINKED (45000 MPA.S); ISOPROPYL PALMITATE

Divine Derrier Skin Bleaching Cream

Active Ingredient Purpose

Hydroquinone 2% Skin lightener

Uses

- Lightens skin discoloration sich as freckles, age and liver spots or pigment in the skin that may occur in pregnancy or from the use of oral contraceptions

Keep out of children

If swallowed, get medical help or contact a Poison Control Center immediately.

Stop use and ask a doctor

- If rash occurs

Warnings: for external use only

When using this product

- Avoid contact with eyes
- Limit sun exposure. Protect skin with a Broad-Spectrum sunscreen agent, wear protective clothing to cover bleached skin after treatment to prevent darkening from reoccuring
- Some users of this product may experience mild irritation. If skin irritation becomes severe, stop use and consult a physician
- Do not use on children under 12 years of age unless directed by a physician
- If product consult with a doctor before use
- If pregnant or breast-feeding
- Speak with a healthcare professional before use

Sunburn alert

- This product contains an alpha-hydroxy acid (AHA) that may increase your skin's sensitivity to the sun and particularly the possibility of sunburn. Use a sunscreen, wear protective clothing, and limit sun exposure while using this product and for a week afterwards

Directions

Adult apply a small amount

INACTIVE INGREDIENT

Inactive Ingredients Water(Aqua), Isopropyl Palmitate, Caprylic/capric Triglyceride, Cetearyl Alcohol, Glyceryl Stearate, Propanediol, Glycolic Acid, Lactic Acid, Kojic Dipalmitate, Sodium Hydroxide, Polyacrylate Crosspolymer-6, Niacinamide, Allantoin, Ferulic Acid, Butylene Glycol, hydrogenated Lecithin, Sodium Oleate, Oligopeptide-68, Dipotassium Glycrrhizate, Sodium Sulfate, Sodium Metabisulfite, Tocopheryl Acetate, Dimethicone, PEG-40 Stearate, Disodium EDTA, Xanthan Gum, Ethylhexylglycerin, Phenoxyethanol, Frangrance.

PACKAGE LABEL

Divine Derriere Skin Bleaching Cream

Hydroquinone 2% Skin Lightener

50 ml - 1.7fl oz